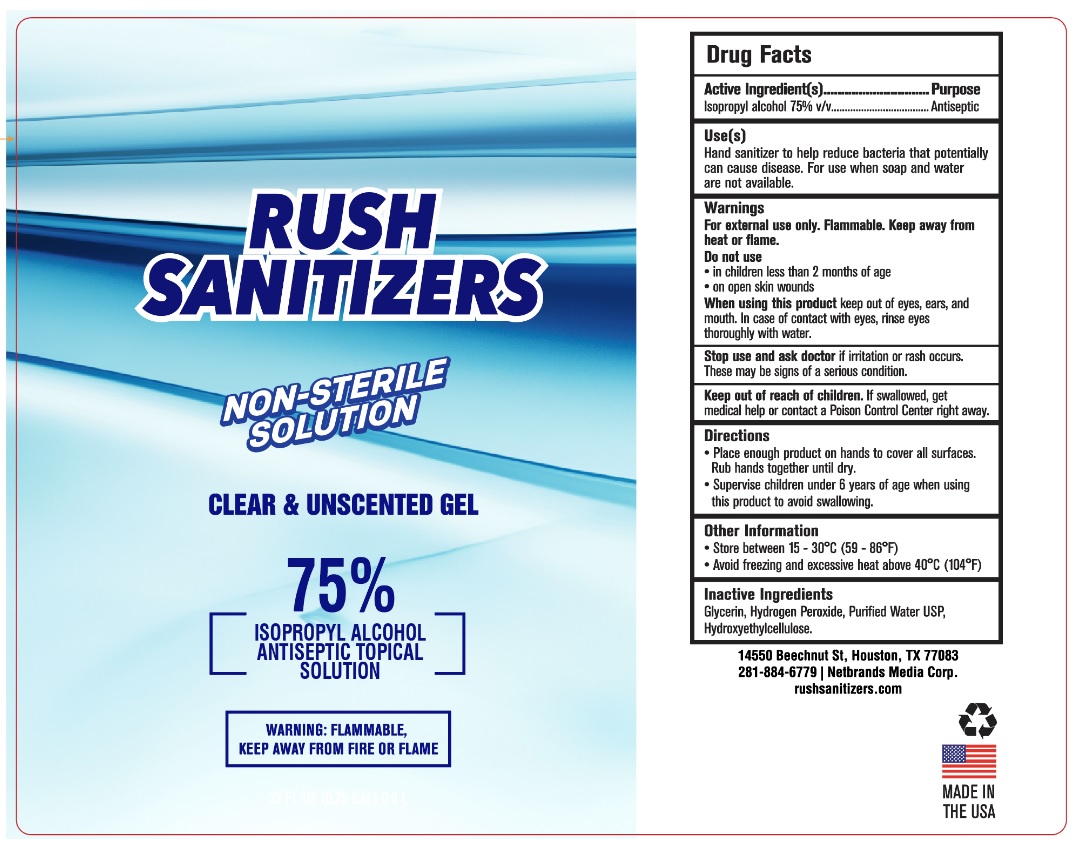 DRUG LABEL: Rush Sanitizers
NDC: 74599-175 | Form: GEL
Manufacturer: Netbrands Media Corp
Category: otc | Type: HUMAN OTC DRUG LABEL
Date: 20200421

ACTIVE INGREDIENTS: ISOPROPYL ALCOHOL 75 mL/100 mL
INACTIVE INGREDIENTS: GLYCERIN; HYDROGEN PEROXIDE; WATER; HYDROXYETHYL CELLULOSE, UNSPECIFIED

Rush Sanitizers

Active Ingredient(s)

Isopropyl alcohol 75% v/v

Purpose

Antiseptic

Use(s)

Hand sanitizer to help reduce bacteria that potentially can cause disease. For use when soap and water are not available.

Warnings

For external use only. Flammable. Keep away from heat or flame.

Do not use

- in children less than 2 months of age
- on open skin wounds

When using this product keep out of eyes, ears, and mouth. In case of contact with eyes, rinse eyes thoroughly with water.

Stop use and ask doctor if irritation or rash occurs. These may be signs of a serious condition.

Keep out of reach of children. If swallowed, get medical help or contact a Poison Control Center right away.

Directions

- Place enough product on hands to cover all surfaces. Rub hands together until dry.
- Supervise children under 6 years of age when using this product to avoid swallowing.

Other Information

- Store between 15 - 30°C (59 - 86°F)
- Avoid freezing and excessive heat above 40°C (104°F)

Inactive Ingredients

Glycerin, Hydrogen Peroxide, Purified Water USP, Hydroxyethylcellulose.

NON-STERILE SOLUTION

CLEAR & UNSCENTED GEL

ANTISEPTIC TOPICAL SOLUTION

WARNING:FLAMMABLE, KEEP AWAY FROM FIRE OR FLAME

14550 Beechnut St, Houston, TX 77083

281-884-6779 | Netbrands Media Corp.

rushsanitizers.com

MADE IN THE USA